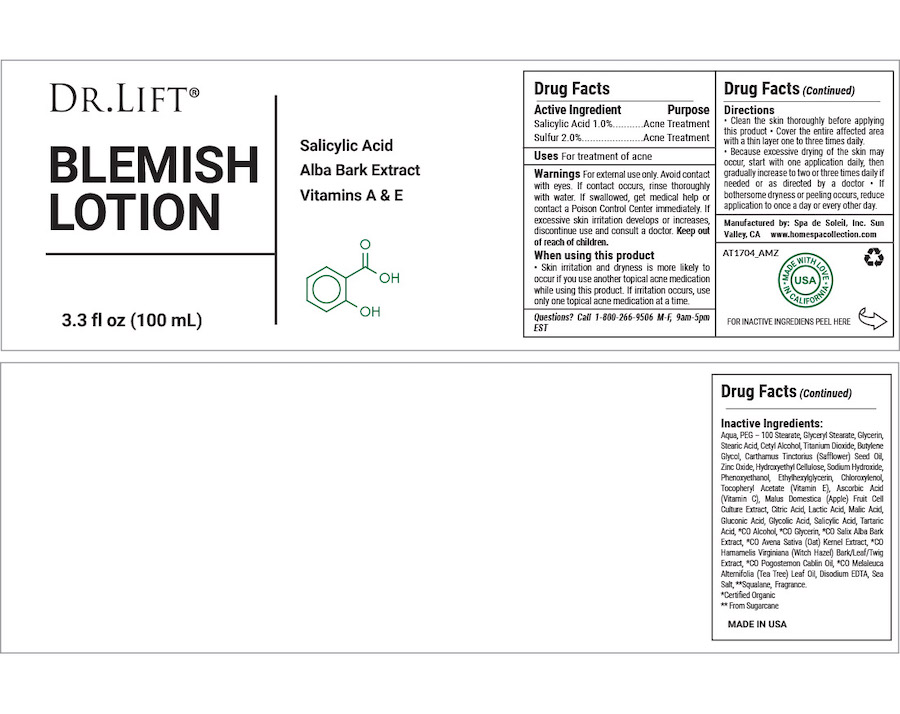 DRUG LABEL: Dr Lift Blemish
NDC: 68062-2265 | Form: LOTION
Manufacturer: Spa de Soleil
Category: otc | Type: HUMAN OTC DRUG LABEL
Date: 20260121

ACTIVE INGREDIENTS: SULFUR 2 mg/100 mL; SALICYLIC ACID 1 mg/100 mL
INACTIVE INGREDIENTS: PEG-100 STEARATE; GLYCERYL STEARATE/PEG-100 STEARATE; GLYCERIN; STEARIC ACID D7; CETYL ALCOHOL; WATER

Dr Lift Blemish Lotion

Active ingredient Purpose

Salicylic Acid (0.5%)..........Acne Treatment

Sulfur (2.0%)......................Acne Treatment

Purpose

Acne Treatment

INDICATIONS AND USAGE

For treatment of acne

Warnings

For external use only

Avoid contact with eyes. If contact occurs, rinse thoroughly with water.

If swallowed, get medical help or contact a Poison Control Center right away. If excessive skin irritation develops or increases, discontinue use and consult a doctor. Keep out of reach of children.

Keep out of reach of children. In case of accidental ingestion, get medical help or contact a Poison Control Center right away.

When using this product

• Skin irritation and dryness is more likely to occur if you use another topical acne medication while using this product. If irritation occurs, use only one topical acne medication at a time.

Directions

• Clean the skin thoroughly before applying this product • Cover the entire affected area with a thin layer one to three times daily.

• Because excessive drying of the skin may occur, start with one application daily, then gradually increase to two or three times daily if needed or as directed by a doctor • If bothersome dryness or peeling occurs, reduce application to once a day or every other day.

INACTIVE INGREDIENT

Other Ingredients:

Aqua, PEG – 100 Stearate, Glyceryl Stearate, Glycerin, Stearic Acid, Cetyl Alcohol, Titanium Dioxide, Butylene Glycol, Carthamus Tinctorius (Safflower) Seed Oil, Zinc Oxide, Hydroxyethyl Cellulose, Sodium Hydroxide, Phenoxyethanol, Ethylhexylglycerin, Chloroxylenol, Tocopheryl Acetate (Vitamin E), Ascorbic Acid (Vitamin C), Malus Domestica (Apple) Fruit Cell Culture Extract, Citric Acid, Lactic Acid, Malic Acid, Gluconic Acid, Glycolic Acid, Salicylic Acid, Tartaric Acid, *CO Alcohol, *CO Glycerin, *CO Salix Alba Bark Extract, *CO Avena Sativa (Oat) Kernel Extract, *CO Hamamelis Virginiana (Witch Hazel) Bark/Leaf/Twig Extract, *CO Pogostemon Cablin Oil, *CO Melaleuca Alternifolia (Tea Tree) Leaf Oil, Disodium EDTA, Sea Salt, **Squalane, Fragrance.